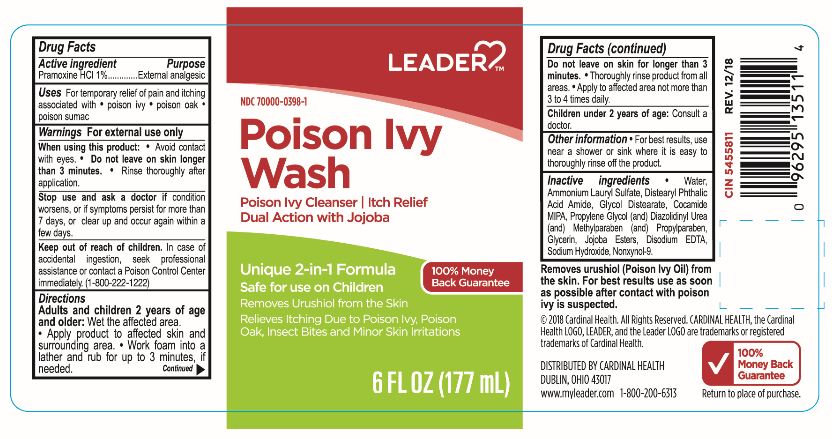 DRUG LABEL: Leader Poison Ivy Wash
NDC: 70000-0398 | Form: LOTION
Manufacturer: Cardinal Health, 110 dba Leader
Category: otc | Type: HUMAN OTC DRUG LABEL
Date: 20240513

ACTIVE INGREDIENTS: PRAMOXINE HYDROCHLORIDE 10 mg/1 mL
INACTIVE INGREDIENTS: AMMONIUM LAURYL SULFATE; PROPYLPARABEN; GLYCOL DISTEARATE; GLYCERIN; PROPYLENE GLYCOL; SODIUM HYDROXIDE; EDETATE DISODIUM; NONOXYNOL-9; DIAZOLIDINYL UREA; WATER; METHYLPARABEN; HYDROLYZED JOJOBA ESTERS (ACID FORM)

LEADER Poison Ivy Wash

When using this product:

- avoid contact with eyes
- do not leave on skin longer than 3 minutes
- rinse thoroughly after application

Inactive Ingredients:

Water

Ammonium Lauryl Sulfate

Distearyl Phthalic Acid Amide

Glycol Distearate

Cocamide MIPA

Propylene Glycol

Diazolidinyl Urea

Methylparaben

Propylparaben Glycerin

Jojoba Esters

Disodium EDTA

Sodium Hydroxide

Nonxynol-9

DOSAGE AND ADMINISTRATION

Adults and children 2 years of age and older:

- Wet the affected area
- Apply product to affected skin and surrounding area
- work foam into a lather and rub for up to 3 minutes, if needed

INDICATIONS AND USAGE

For temporary relief of pain and itching associated with poison ivy, poison oak, poison sumac.

Keep out of reach of children. In case of accidental ingestion, week professional assistance or contact a poison control center immediately. (1-800-222-1222)

PURPOSE

External Analgesic

ACTIVE INGREDIENT

Pramoxine HCl 1%